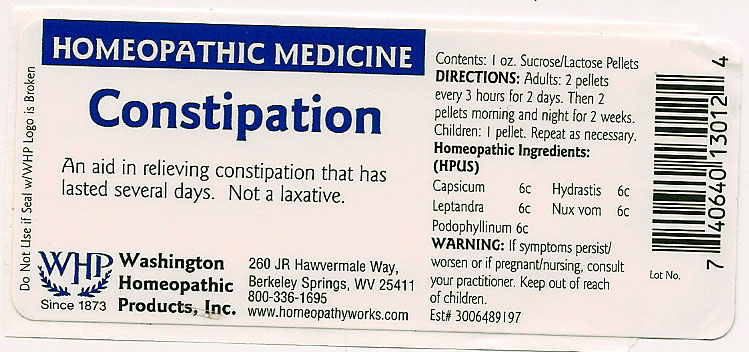 DRUG LABEL: Constipation
NDC: 68428-010 | Form: PELLET
Manufacturer: Washington Homeopathic Products
Category: homeopathic | Type: HUMAN OTC DRUG LABEL
Date: 20191223

ACTIVE INGREDIENTS: CAPSICUM 6 [hp_C]/28 g; GOLDENSEAL 6 [hp_C]/28 g; VERONICASTRUM VIRGINICUM ROOT 6 [hp_C]/28 g; STRYCHNOS NUX-VOMICA SEED 6 [hp_C]/28 g; PODOPHYLLUM RESIN 6 [hp_C]/28 g
INACTIVE INGREDIENTS: SUCROSE; LACTOSE

DRUG FACTS

ACTIVE INGREDIENTS

CAPSIUM 6C

HYDRASTIS CAN 6C

LEPTANDRA 6C

NUX VOM 6C

PODOPHYLLINUM 6C

USES

To relieve the symptoms of constipation that has lasted several days. Not a laxative.

KEEP OUT OF REACH OF CHILDREN

Keep this and all medicines out of reach of children.

INDICATIONS

CAPSIUM Fever

HYDRASTIS CAN Sinuses

LEPTANDRA Constipation

NUX VOM Vomiting

PODOPHYLLINUM Diarrhea

STOP USE AND ASK DOCTOR

If symptoms persist/worsen or if pregnant/nursing, stop use and consult your practitioner.

DIRECTIONS

Adults 2 pellets every 3 hours for 2 days. Then 2 pellets morning and night for 2 weeks.

Children: 1 pellet. Repeat as necessary.

INACTIVE INGREDIENTS

Sucrose/Lactose

PRINCIPAL DISPLAY PANEL

Enter section text here